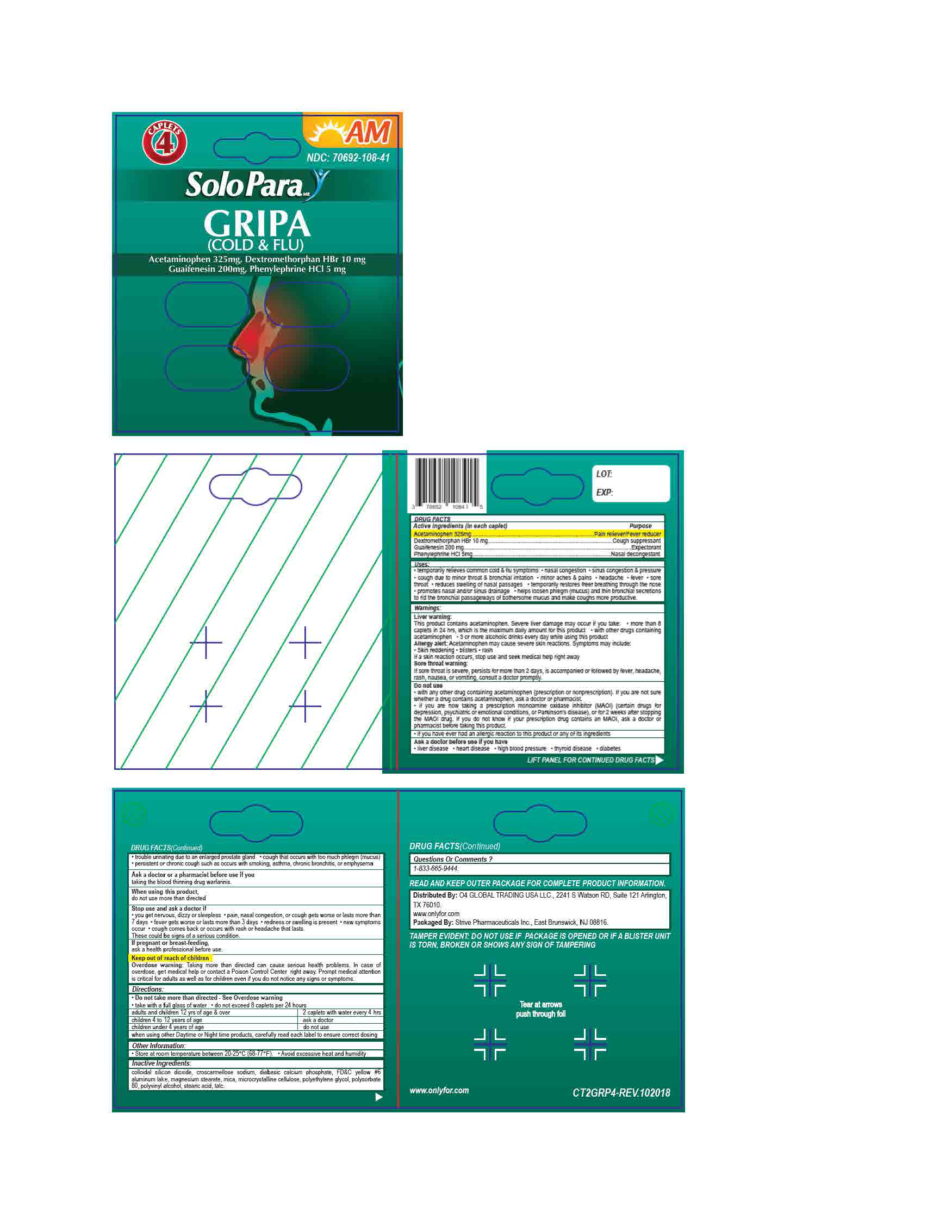 DRUG LABEL: Acetaminophen 500mg, Dextromethorphan HBr 10mg, Guaifenesin 200mg, Phenylephrine HCl 5mg
NDC: 70692-108 | Form: TABLET
Manufacturer: Strive Pharmaceuticals Inc
Category: otc | Type: HUMAN OTC DRUG LABEL
Date: 20201116

ACTIVE INGREDIENTS: GUAIFENESIN 200 mg/1 1; PHENYLEPHRINE HYDROCHLORIDE 5 mg/1 1; DEXTROMETHORPHAN HYDROBROMIDE 10 mg/1 1; ACETAMINOPHEN 325 mg/1 1
INACTIVE INGREDIENTS: STEARIC ACID; CROSCARMELLOSE SODIUM; POLYETHYLENE GLYCOL 400; FD&C YELLOW NO. 6; DIBASIC CALCIUM PHOSPHATE DIHYDRATE; MICROCRYSTALLINE CELLULOSE; SILICON DIOXIDE; MICA; MAGNESIUM STEARATE; POLYSORBATE 80; TALC; POLYVINYL ALCOHOL, UNSPECIFIED

Cold & Flu - Gripa (Acetaminophen 325mg; Dextromethorphan HBr 10mg, Guaifenesin 200mg, Phenylephrine HCl 5mg)

ACTIVE INGREDIENT

Acetaminophen 325mg; Dextromethorphan HBr 10mg; Gauifenesin 200mg; Phenylephrine HCl 5mg

INACTIVE INGREDIENT

colloidal silicon dioxide, croscarmellose sodium, dibasic calcium phosphate, FD&C yellow#6, magnesium staerate, mica, microcrystalline cellulose, polyethylene glycol, polysorbate 80, polyvinyl alcohol, stearic acid, talc

DOSAGE AND ADMINISTRATION

- take with a full glass of water
- do not take more than directed
- do not exceed 8 caplets per 24 hours

adults & children 12 years of age & over | 2 caplets with water every 4 hours
children 4 to 12 years of age | ask a doctor
children under 4 years of age | do not use

INDICATIONS AND USAGE

*temporarily relief of occasional heaches and minor aches and pains with accompanying sleeplessness

WARNINGS

Liver warning:

This product contains acetaminophen. Severe liver damage may occur if you take:

- more than 8 caplets in 24 hours, which is the maximum daily amount for this product
- with other drugs containing acetaminophen
- 3 or more alcoholic drinks every day while using this product

Allergy alert:

Acetaminophen may cause severe skin reactions. Symptoms may include:

- skin reddening
- blisters
- rash

if a skin reaction occurs, stop use and seek medical help right away

Sore throat warning:

If sore throat is severe, persists for more than 2 days, is accompanied or followed by fever, headache, rash, nausea, or vomiting, consult a doctor promptly

Do not use

- with any other drug containing acetaminophen (prescription or non prescription). If you are not sure whether a drug contains acetaminophen, ask a doctor or pharmacist
- if you are now taking a prescription monoamine oxidase inhibitor (MAOI) (certain drugs for depression, psychiatric or emotional conditions, or Parkinson's disease), or for 2 weeks after stopping the MAOI drug. If you do not know if your prescription drug contains an MAOI, ask a doctor or pharmacist before taking ths product
- if you have ever had an allergic reaction to this product or any of its ingredients

Ask a doctor before use if you have

- liver disease
- heart disease
- high blood pressure
- thyroid disease
- diabetes
- trouble urinating due to an enlarged prostrate gland
- cough that occurs with too much phlegm (mucus)
- persistent or chronic cough such as occurs with smoking, asthama, chronic bronchitis, or emphysema

Ask a doctor or a pharmacist before use if you are

- taking the blood thinning drug warfarin

When using this product

- do not use more than directed

Stop use and ask a doctor if

- you get nervous, dizzy or sleepless
- pain, nasal congestion, or cough gets worse or lasts more than 7 days
- fever gets worse or lasts more than 3 days
- redness or swelling is present
- new symptoms occur
- cough comes back or occurs with rash or headache that lasts

These could be signs of a serious condition

If pregnant or breast-feeding,

ask a health professional before use

Keep out of reach of children

Overdose warning: In case of accidental overdose, get medical help or contact a Poison Control Center right away. Prompt medical attention is critical for adults as well as for children even if you do not notice any signs or symptoms.

Keep out of reach of children

Overdose Warning: In case of accidental overdose, get medical help or contact a Poison Control Center right away. Prompt medical attention is critical for adults as well as for children even if you do not notice any signs or symptoms.

PURPOSE

Pain reliever / fever reducer, cough suppressant, expectorant, nasal decongestant

OTHER SAFETY INFORMATION

- store at room temperature between 20ºC - 25ºC (68ºF - 77ºF)
- avoid excessive heat and humidity